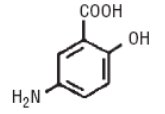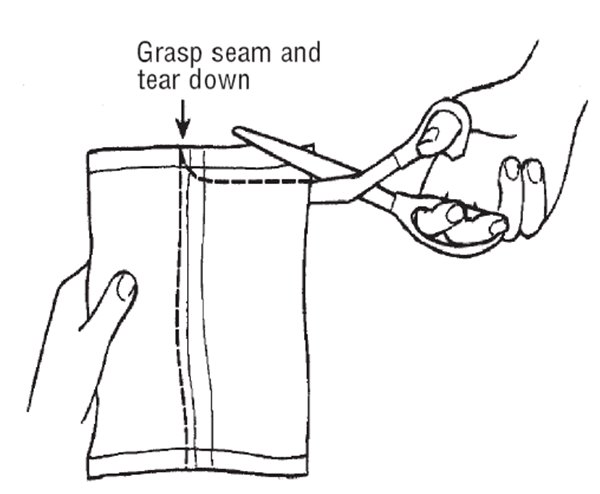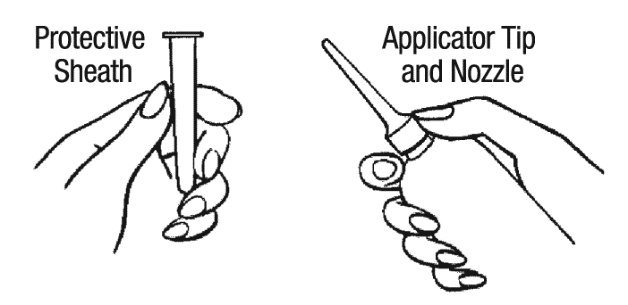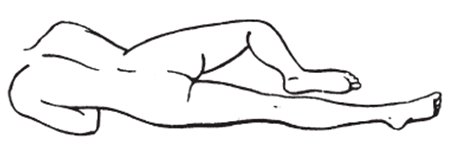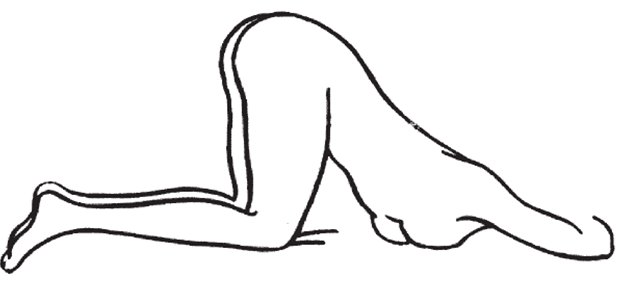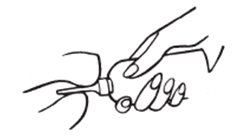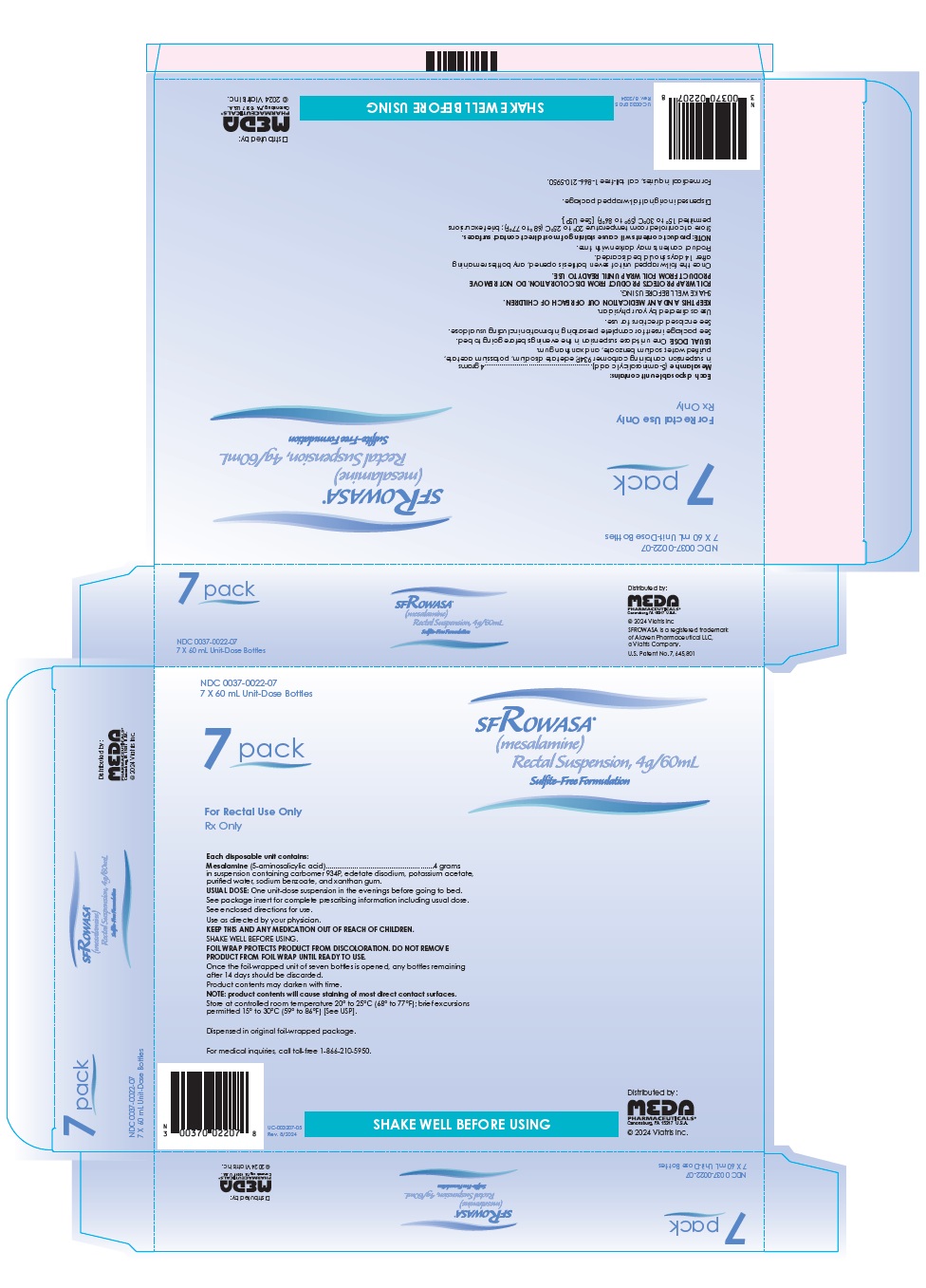 DRUG LABEL: sfRowasa
NDC: 0037-0022 | Form: SUSPENSION
Manufacturer: Viatris Specialty LLC
Category: prescription | Type: HUMAN PRESCRIPTION DRUG LABEL
Date: 20240724

ACTIVE INGREDIENTS: MESALAMINE 4 g/60 mL
INACTIVE INGREDIENTS: CARBOMER HOMOPOLYMER TYPE B (ALLYL PENTAERYTHRITOL OR ALLYL SUCROSE CROSSLINKED); EDETATE DISODIUM; POTASSIUM ACETATE; WATER; SODIUM BENZOATE; XANTHAN GUM

HIGHLIGHTS OF PRESCRIBING INFORMATION

These highlights do not include all the information needed to use sfROWASA safely and effectively. See full prescribing information for sfROWASA.
sfROWASA® (mesalamine) rectal suspension sulfite-free formulation
Initial U.S. Approval: 1987

1 INDICATIONS AND USAGE

sfROWASA is an aminosalicylate indicated for treatment of active mild to moderate distal ulcerative colitis, proctosigmoiditis or proctitis in adults. (1)

2 DOSAGE AND ADMINISTRATION

- Evaluate renal function prior to initiation of sfROWASA and periodically while on therapy. (2, 5.1)
- The recommended dosage is one rectal instillation (4 grams) once a day, preferably at bedtime, and retained for approximately eight hours for 3 to 6 weeks depending on symptoms and sigmoidoscopic findings. (2)
- Drink an adequate amount of fluids. (2. 5.7)

3 DOSAGE FORMS AND STRENGTHS

Rectal Suspension: 4 g/60 mL suspension bottle (3)

4 CONTRAINDICATIONS

Known or suspected hypersensitivity to salicylates, aminosalicylates or any other of the ingredients in sfROWASA. (4, 5.1)

5 WARNINGS AND PRECAUTIONS

- Renal Impairment: Assess renal function at the beginning of treatment and periodically during treatment. Evaluate the risks and benefits of sfROWASA in patients with known renal impairment or taking nephrotoxic drug. Discontinue sfROWASA if renal function deteriorates while on therapy. (7.1)
- Mesalamine-Induced Acute Intolerance Syndrome: Discontinue treatment if acute intolerance syndrome (cramping, acute abdominal pain, bloody diarrhea, sometimes fever, headache and rash) is suspected. (5.2)
- Hepatic Failure: Evaluate the risks and benefits of using sfROWASA in patients with known liver impairment. (5.3)
- Severe Cutaneous Adverse Reactions: Discontinue at the first signs or symptoms of severe cutaneous adverse reactions or other sings of hypersensitivity and consider further evaluation. (5.4)
- Photosensitivity: Avoid sun exposure if pre-existing skin conditions. (5.5)
- Nephrolithiasis: Cases of nephrolithiasis have been reported with the use of mesalamine. Mesalamine-containing stones are undetectable by standard radiography or computed tomography (CT). Ensure adequate hydration during treatment. (5.6)
- Interference with Laboratory Tests: Mesalamine may lead to elevated urinary normetanephrine test results. (5.7)

6 ADVERSE REACTIONS

Most common adverse reactions (≥1%) are: gas/flatulence, flu, fever, leg/joint pain, hemorrhoids, rectal pain and hair loss. (6.1)

To report SUSPECTED ADVERSE REACTIONS, contact Meda Pharmaceuticals Inc at 1-866-210-5949 or FDA at 1-800-FDA-1088 or www.fda.gov/medwatch.

7 DRUG INTERACTIONS

- Nephrotoxic Agents including Non-Steroidal Anti-inflammatory Drugs (NSAIDs): Increased risk of nephrotoxicity; monitor for changes in renal function and mesalamine-related adverse reactions. (7.1)
- Azathioprine or 6-Mercaptopurine: Increased risk of blood dyscrasias; monitor complete blood cell counts and platelet counts. (7.2)

8 USE IN SPECIFIC POPULATIONS

Geriatric Patients: Increased risk of blood dyscrasias; monitor complete blood cell counts and platelet counts. (8.5)

FULL PRESCRIBING INFORMATION

1 INDICATIONS AND USAGE

sfROWASA is indicated for the treatment of active mild to moderate distal ulcerative colitis, proctosigmoiditis or proctitis in adults.

2 DOSAGE AND ADMINISTRATION

Evaluate renal function before initiating therapy with sfROWASA [see Warnings and Precautions (5.1)].

Recommended Dosage

The recommended dosage is one rectal instillation (4 grams) once a day, preferably at bedtime, and retained for approximately eight hours for 3 to 6 weeks depending on symptoms and sigmoidoscopic findings.

Administration Instructions

- Shake the bottle to ensure the suspension is homogeneous.
- Remove the protective sheath from the applicator tip.
- Assume the correct body position:
  - Lie on the left side with the lower leg extended and the upper right leg flexed forward for balance.
  - Alternatively, sit in the knee to chest position.
- Gently insert the applicator tip in the rectum pointing toward the umbilicus.
- Steadily squeeze the bottle to discharge the medication.
- Remain in the position for at least 30 minutes. Administer at bedtime with the objective of retaining it all night.
- Drink an adequate amount of fluids during treatment [see Warnings and Precautions (5.7)].

3 DOSAGE FORMS AND STRENGTHS

Rectal Suspension: 4 g/60 mL suspension bottle; off-white to tan colored suspension

4 CONTRAINDICATIONS

sfROWASA is contraindicated in patients with known or suspected hypersensitivity to salicylates, aminosalicylates or any other component of this medication [see Warnings and Precautions (5.3)].

5 WARNINGS AND PRECAUTIONS

5.1 Renal Impairment

Renal impairment, including minimal change disease, acute and chronic interstitial nephritis, and renal failure have been reported in patients given sfROWASA or other products that contain mesalamine or are converted to mesalamine. In animal studies, the kidney was the principal organ of mesalamine toxicity [see Nonclinical Toxicology (13.2)].

Evaluate the risks and benefits of using sfROWASA in patients with known renal impairment or a history of renal disease or taking concomitant nephrotoxic drugs. Evaluate renal function in all patients prior to initiation and periodically while on sfROWASA therapy. Discontinue sfROWASA if renal function deteriorates while on therapy [see Drug Interactions (7.1), Use in Specific Populations (8.6)].

5.2 Mesalamine-Induced Acute Intolerance Syndrome

Mesalamine has been associated with an acute intolerance syndrome that may be difficult to distinguish from a flare of inflammatory bowel disease. Although the exact frequency of occurrence cannot be ascertained, it has occurred in 3% of patients in controlled clinical trials of mesalamine or sulfasalazine. Symptoms include cramping, acute abdominal pain and bloody diarrhea, sometimes fever, headache, and rash. Monitor patients for worsening of these symptoms while on treatment. If acute intolerance syndrome is suspected, promptly discontinue treatment with sfROWASA.

5.3 Hepatic Failure

There have been reports of hepatic failure in patients with pre-existing liver disease who have been administered other products containing mesalamine. Evaluate the risks and benefits of using sfROWASA in patients with known liver impairment.

5.4 Severe Cutaneous Adverse Reactions

Severe cutaneous adverse reactions, including Stevens-Johnson syndrome (SJS) and toxic epidermal necrolysis (TEN), drug reaction with eosinophilia and systemic symptoms (DRESS), and acute generalized exanthematous pustulosis (AGEP) have been reported with the use of mesalamine [see Adverse Reactions (6)]. Discontinue sfROWASA at the first signs or symptoms of severe cutaneous adverse reactions or other signs of hypersensitivity and consider further evaluation.

5.5 Photosensitivity

Patients with pre-existing skin conditions such as atopic dermatitis and atopic eczema have reported more severe photosensitivity reactions. Advise patients to avoid sun exposure, wear protective clothing, and use a broad-spectrum sunscreen when outdoors.

5.6 Nephrolithiasis

Cases of nephrolithiasis have been reported with the use of mesalamine, including stones with 100% mesalamine content. Mesalamine-containing stones are radiotransparent and undetectable by standard radiography or computed tomography (CT). Ensure adequate fluid intake during treatment.

5.7 Interference with Laboratory Tests

Use of mesalamine may lead to spuriously elevated test results when measuring urinary normetanephrine by liquid chromatography with electrochemical detection because of the similarity in the chromatograms of normetanephrine and the main metabolite of mesalamine, N‑acetyl‑5‑aminosalicylic acid (N‑Ac‑5‑ASA). Consider an alternative, selective assay for normetanephrine.

6 ADVERSE REACTIONS

The following clinically significant adverse reactions are described elsewhere in the labeling:

- Renal impairment [see Warnings and Precautions (5.1)]
- Mesalamine-induced acute intolerance syndrome [see Warnings and Precautions (5.2)]
- Hepatic failure [see Warnings and Precautions (5.3)]
- Severe cutaneous adverse reactions [see Warnings and Precautions (5.4)]
- Photosensitivity [see Warnings and Precautions (5.5)]
- Nephrolithiasis [see Warnings and Precautions (5.6)]

6.1 Clinical Trials Experience

Because clinical trials are conducted under widely varying conditions, adverse reaction rates observed in the clinical trials of a drug cannot be directly compared to rates in the clinical trials of another drug and may not reflect the rates observed in practice.

Table 1: Adverse Reactions [reported in 1% or more of sfROWASA-treated patients and greater than placebo] in Clinical Trials of sfROWASA in Adult Patients with Ulcerative Colitis, Proctosigmoiditis or Proctitis
Adverse Reaction | sfROWASA; (N=815); % | Placebo; (N=128); %
Gas/Flatulence | 6 | 4
Flu | 5 | 1
Fever | 3 | 0
Leg/Joint pain | 2 | 1
Hemorrhoids | 1 | 1
Rectal pain | 1 | 0
Hair loss | 1 | 0

6.2 Postmarketing Experience

The following adverse reactions have been identified during post-approval use of mesalamine. Because these reactions are reported voluntarily from a population of uncertain size, it is not always possible to reliably estimate their frequency or establish a causal relationship to drug exposure.

Gastrointestinal Disorders: pancreatitis

Hematologic Disorders: agranulocytosis, aplastic anemia, eosinophilia, leukopenia, neutropenia, pancytopenia, thrombocytopenia

Hepatic Disorders: elevated liver enzymes, hepatic failure [see Warnings and Precautions (5.3)]

Nervous System: intracranial hypertension

Renal and Urinary Disorders: acute renal failure, chronic renal failure, interstitial nephritis, nephrogenic diabetes insipidus, nephrolithiasis, nephrotoxicity [see Warnings and Precautions (5.1), (5.6)]

- Urine discoloration occurring ex-vivo caused by contact of mesalamine including inactive metabolite, with surfaces or water treated with hypochlorite-containing bleach

Reproductive System and Breast Disorders: reversible oligospermia

Respiratory, Thoracic, and Mediastinal Disorders: fibrosing alveolitis, pleurisy/pleuritis

Skin and Subcutaneous Tissue Disorders: AGEP, DRESS, SJS/TEN [see Warnings and Precautions (5.4)]

7 DRUG INTERACTIONS

7.1 Nephrotoxic Agents, Including Non-Steroidal Anti-Inflammatory Drugs

The concurrent use of mesalamine with known nephrotoxic agents, including non-steroidal anti-inflammatory drugs (NSAIDs), may increase the risk of nephrotoxicity. Monitor patients taking nephrotoxic drugs for changes in renal function and mesalamine-related adverse reactions [see Warnings and Precautions (5.2)].

7.2 Azathioprine or 6-Mercaptopurine

The concurrent use of mesalamine with azathioprine or 6‑mercaptopurine and/or any other drugs known to cause myelotoxicity may increase the risk for blood disorders, bone marrow failure, and associated complications. If concomitant use of sfROWASA and azathioprine or 6-mercaptopurine cannot be avoided, monitor blood tests, including complete blood cell counts and platelet counts.

7.3 Interference with Urinary Normetanephrine Measurements

Use of sfROWASA may lead to spuriously elevated test results when measuring urinary normetanephrine by liquid chromatography with electrochemical detection [see Warnings and Precautions (5.7)]. Consider an alternative, selective assay for normetanephrine.

8 USE IN SPECIFIC POPULATIONS

8.1 Pregnancy

Risk Summary

Published data from meta-analyses, cohort studies and case series on the use of mesalamine during pregnancy have not reliably informed an association with mesalamine and major birth defects, miscarriage, or adverse maternal or fetal outcomes (see Data). There are adverse effects on maternal and fetal outcomes associated with ulcerative colitis in pregnancy (see Clinical Considerations). In animal reproduction studies, rats and rabbits administered mesalamine during organogenesis at oral doses up to 5 and 8 times the maximum recommended human dose, respectively, did not reveal any evidence of harm to the embryo or the fetus (see Data).

The background risk of major birth defects and miscarriage for the indicated population is unknown. All pregnancies have a background risk of birth defect, loss, or other adverse outcomes. In the U.S. general population, the estimated background risk of major birth defects and miscarriage in clinically recognized pregnancies is 2% to 4% and 15% to 20%, respectively.

Clinical Considerations

Disease-associated maternal and embryo/fetal risk

Published data suggest that increased disease activity is associated with the risk of developing adverse pregnancy outcomes in women with ulcerative colitis. Adverse pregnancy outcomes include preterm delivery (before 37 weeks of gestation), low birth weight (less than 2500 g) infants, and small for gestational age at birth.

Data

Human Data

Published data from meta-analyses, cohort studies and case series on the use of mesalamine, the active moiety of sfROWASA, during early pregnancy (first trimester) and throughout pregnancy have not reliably informed an association of mesalamine and major birth defects, miscarriage, or adverse maternal or fetal outcomes. There is no clear evidence that mesalamine exposure in early pregnancy is associated with an increase risk in major congenital malformations, including cardiac malformations. Published epidemiologic studies have important methodological limitations which hinder interpretation of the data, including inability to control for confounders, such as underlying maternal disease, and maternal use of concomitant medications, and missing information on the dose and duration of use for mesalamine products.

Animal Data

Reproduction studies have been performed with mesalamine in rats and rabbits during organogenesis at oral doses up to 5 and 8 times respectively, the maximum recommended human dose, and have revealed no evidence of harm to the embryo or the fetus.

8.2 Lactation

Risk Summary

Data from published literature report the presence of mesalamine and its metabolite, N‑acetyl‑5‑aminosalicylic acid in human milk in small amounts with relative infant doses (RID) of 0.1% or less for mesalamine (see Data). There are case reports of diarrhea observed in breastfed infants exposed to mesalamine (see Clinical Considerations). There is no information on the effects of mesalamine on milk production. The lack of clinical data during lactation precludes a clear determination of the risk of sfROWASA to an infant during lactation; therefore, the developmental and health benefits of breastfeeding should be considered along with the mother’s clinical need for sfROWASA and any potential adverse effects on the breastfed child from sfROWASA or from the underlying maternal condition.

Clinical Considerations

Advise the caregiver to monitor the breastfed infant for diarrhea.

Data

In published lactation studies, maternal mesalamine doses from various oral and rectal formulations and products ranged from 500 mg to 4.8 g daily. The average concentration of mesalamine in milk ranged from non‑detectable to 0.5 mg/L. The average concentration of N‑acetyl‑5-aminosalicylic acid in milk ranged from 0.2 to 9.3 mg/L. Based on these concentrations, estimated infant daily dosages for an exclusively breastfed infant are 0 to 0.075 mg/kg/day of mesalamine (RID 0% to 0.1%) and 0.03 to 1.4 mg/kg/day of N‑acetyl‑5‑aminosalicylic acid.

8.4 Pediatric Use

Safety and effectiveness in pediatric patients have not been established.

8.5 Geriatric Use

Clinical trials of sfROWASA did not include sufficient numbers of patients aged 65 years and over to determine whether they respond differently from younger patients. Reports from uncontrolled clinical studies and postmarketing reporting systems suggested a higher incidence of blood dyscrasias (i.e., agranulocytosis, neutropenia and pancytopenia) in patients receiving mesalamine-containing products such as sfROWASA who were 65 years or older compared to younger adult patients, which may also be associated with ulcerative colitis, use of interacting drugs, or reduced renal function.

Consider monitoring complete blood cell counts and platelet counts in patients 65 years and over during treatment with sfROWASA. In general, consider the greater frequency of decreased hepatic, renal, or cardiac function, and of concurrent disease or other drug therapy in patients 65 years and over when prescribing sfROWASA.

8.6 Renal Impairment

Mesalamine is known to be substantially excreted by the kidney, and the risk of toxic reactions may be greater in patients with impaired renal function. Evaluate renal function in all patients prior to initiation and periodically while on sfROWASA therapy. Monitor patients with known renal impairment or history of renal disease or taking nephrotoxic drugs for decreased renal function and mesalamine-related adverse reactions. Discontinue sfROWASA if renal function deteriorates while on therapy [see Warnings and Precautions (5.2)].

10 OVERDOSAGE

sfROWASA is an aminosalicylate, and symptoms of salicylate toxicity include nausea, vomiting and abdominal pain, tachypnea, hyperpnea, tinnitus, and neurologic symptoms (headache, dizziness, confusion, seizures). Severe salicylate intoxication may lead to electrolyte and blood pH imbalance and potentially to other organ (e.g., renal and liver) involvement.

There is no specific antidote for mesalamine overdose; however, conventional therapy for salicylate toxicity may be beneficial in the event of acute overdosage and may include gastrointestinal tract decontamination to prevent further absorption. Correct fluid and electrolyte imbalance by the administration of appropriate intravenous therapy and maintain adequate renal function.

11 DESCRIPTION

The active ingredient in sfROWASA® (mesalamine) Rectal Suspension, a disposable (60 mL) unit, is mesalamine, also known as 5-aminosalicylic acid (5-ASA). Chemically, mesalamine is 5-amino-2-hydroxybenzoic acid.

The empirical formula is C7H7NO3, representing a molecular weight of 153.14. The structural formula is:

sfROWASA is supplied as a suspension for rectal administration. Each rectal suspension unit contains 4 grams of mesalamine. The inactive ingredients are carbomer 934P, edetate disodium, potassium acetate, purified water, sodium benzoate and xanthan gum. Sodium benzoate is added as a preservative. The disposable unit consists of an applicator tip protected by a polyethylene cover and lubricated with USP white petrolatum. The unit has a one-way valve to prevent back flow of the dispensed product.

12 CLINICAL PHARMACOLOGY

12.1 Mechanism of Action

The mechanism of action of 5-ASA (mesalamine) is not fully understood, but appears to be a topical anti-inflammatory effect on colonic epithelial cells. Mucosal production of arachidonic acid metabolites, both through the cyclooxygenase pathways (i.e., prostanoids), and through the lipoxygenase pathways (i.e., leukotrienes and hydroxyeicosatetraenoic acids) is increased in patients with ulcerative colitis, and it is possible that mesalamine diminishes inflammation by blocking cyclooxygenase and inhibiting prostaglandin production in the colon.

12.2 Pharmacodynamics

The exposure-response relationship and time course of pharmacodynamic response for the safety and effectiveness of mesalamine have not been fully characterized.

12.3 Pharmacokinetics

Absorption

Mesalamine administered rectally as sfROWASA is poorly absorbed from the colon and is excreted principally in the feces during subsequent bowel movements. The extent of absorption is dependent upon the retention time of the drug product, and there is considerable individual variation. Under clinical conditions patients demonstrated plasma levels 10 to 12 hours post mesalamine administration of 2 mcg/mL, about two-thirds of which was the N-acetyl metabolite. In addition, steady state plasma levels demonstrated a lack of accumulation of either parent drug or N-acetyl metabolite during repeated daily rectal administrations.

Distribution

Other than the kidney, the organ distribution and other bioavailability characteristics of absorbed mesalamine in man are not known. The poor colonic absorption of rectally administered mesalamine is substantiated by the low serum concentration of 5-ASA and N-acetyl-5-ASA seen in ulcerative colitis patients after dosage with mesalamine.

Elimination

Metabolism

It is known that the compound undergoes acetylation but whether this process takes place at colonic or systemic sites has not been elucidated.

Excretion

Whatever the metabolic site, most of the absorbed mesalamine is excreted in the urine as the N-acetyl-5-ASA metabolite. At steady state, approximately 10 to 30% of the daily 4-gram dose can be recovered in cumulative 24-hour urine collections. While the elimination half-life of mesalamine is short (0.5 to 1.5 hours), the acetylated metabolite exhibits a half-life of 5 to 10 hours.

13 NONCLINICAL TOXICOLOGY

13.1 Carcinogenesis, Mutagenesis, Impairment of Fertility

Carcinogenesis

In a 2-year carcinogenicity study in Wistar rats fed up to 320 mg/kg/day (approximately 0.78 times the maximum recommended human dose, based on a body surface area comparison). of mesalamine admixed with diet, mesalamine did not cause an increase in the incidence of neoplastic lesions over controls.

Mutagenesis

Mesalamine is not mutagenic to Salmonella typhimurium tester strains TA98, TA100, TA1535, TA1537, TA1538. There were no reverse mutations in an assay using E. coli strain WP2UVRA. There were no evidence of genotoxicity in an in vivo mouse micronucleus assay at 600 mg/kg and in an in vivo sister chromatid exchange assay at doses up to 610 mg/kg.

Impairment of Fertility

Mesalamine had no effects on fertility in rats at doses up to 320 mg/kg/day (approximately 0.78 times the maximum recommended human dose, based on a body surface area comparison).

13.2 Animal Toxicology and/or Pharmacology

Preclinical studies have shown the kidney to be the major target organ for mesalamine toxicity. Adverse renal function changes were observed in rats after a single 600 mg/kg oral dose, but not after a 200 mg/kg dose. Gross kidney lesions, including papillary necrosis, were observed after a single oral >900 mg/kg dose, and after I.V. doses of >214 mg/kg. Mice responded similarly. In a 13-week oral (gavage) dose study in rats, the high dose of 640 mg/kg/day mesalamine caused deaths, probably due to renal failure, and dose-related renal lesions (papillary necrosis and/or multifocal tubular injury) were seen in most rats given the high dose (males and females) as well as in males receiving lower doses 160 mg/kg/day. Renal lesions were not observed in the 160 mg/kg/day female rats. Minimal tubular epithelial damage was seen in the 40 mg/kg/day males and was reversible. In a six-month oral study in dogs, the no-observable dose level of mesalamine was 40 mg/kg/day and doses of 80 mg/kg/day and higher caused renal pathology similar to that described for the rat. In a combined 52-week toxicity and 127-week carcinogenicity study in rats, degeneration in kidneys was observed at doses of 100 mg/kg/day and above admixed with diet for 52 weeks, and at 127 weeks increased incidence of kidney degeneration and hyalinization of basement membranes and Bowman's capsule were seen at 100 mg/kg/day and above. In the 12-month eye toxicity study in dogs, Keratoconjunctivitis Sicca (KCS) occurred at oral doses of 40 mg/kg/day and above. The oral preclinical studies were done with a highly bioavailable suspension where absorption throughout the gastrointestinal tract occurred.

14 CLINICAL STUDIES

In a 6-week placebo-controlled trial, international, multicenter trial of 153 patients with active distal ulcerative colitis, proctosigmoiditis or proctitis, sfROWASA® (mesalamine) rectal suspension reduced the overall disease activity index (DAI) and individual components as follows:

EFFECT OF TREATMENT ON SEVERITY OF DISEASE DATA FROM U.S.-CANADA TRIAL COMBINED RESULTS OF EIGHT CENTERS
Activity Indices, mean
 |  | N | Baseline | Day 22 | End Point | Change Baseline to End Point [* Percent change for overall DAI only (calculated by taking the average of the change for each individual patient).]
Overall DAI | sfROWASA®; Placebo | 76; 77 | 7.42; 7.40 | 4.05 [† Significant sfROWASA®/placebo difference. p < 0.01]; 6.03 | 3.37 [‡ Significant sfROWASA®/placebo difference. p < 0.001]; 5.83 | -55.07%; -21.58%
Stool Frequency | sfROWASA®; Placebo |  | 1.58; 1.92 | 1.11 [§ Significant sfROWASA®/placebo difference. p < 0.05]; 1.47 | 1.01; 1.50 | -0.57; -0.41
Rectal Bleeding | sfROWASA®; Placebo |  | 1.82; 1.73 | 0.59; 1.21 | 0.51; 1.11 | -1.30; -0.61
Mucosal Inflammation | sfROWASA®; Placebo |  | 2.17; 2.18 | 1.22; 1.74 | 0.96; 1.61 | -1.21; -0.56
Physician’s Assessment of Disease Severity | sfROWASA®; Placebo |  | 1.86; 1.87 | 1.13; 1.62 | 0.88; 1.55 | -0.97; -0.30
Each parameter has a 4-point scale with a numerical rating:
0 = normal, 1 = mild, 2 = moderate, 3 = severe. The four parameters are added together to produce a maximum overall DAI of 12.

Differences between sfROWASA® (mesalamine) Rectal Suspension and placebo were also statistically different in subgroups of patients on concurrent sulfasalazine and in those having an upper disease boundary between 5 and 20 or 20 and 40 cm. Significant differences between sfROWASA® (mesalamine) Rectal Suspension and placebo were not achieved in those subgroups of patients on concurrent prednisone or with an upper disease boundary between 40 and 50 cm.

16 HOW SUPPLIED/STORAGE AND HANDLING

sfROWASA® (mesalamine) rectal suspension is an off-white to tan colored suspension. Each disposable suspension bottle contains 4 grams of mesalamine in 60 mL aqueous suspension. Suspension bottles are supplied in boxed, foil-wrapped trays as follows:

NDC 0037-0022-60 .................. Sample – 1 Bottle

NDC 0037-0022-07 .................. Carton of 7 Bottles

NDC 0037-0022-14 .................. Carton of 14 Bottles

NDC 0037-0022-28 .................. Carton of 28 Bottles

sfROWASA® (mesalamine) rectal suspension is for rectal use only.

Storage

Store at controlled room temperature 20°C to 25°C (68°F to 77°F); Excursions permitted to 15°C to 30°C (59°F to 86°F) [see USP Controlled Room Temperature].

Once the foil wrapped unit of seven bottles is opened, all suspensions should be used promptly as directed by your physician. Contents of suspensions removed from the foil pouch may darken with time. Slight darkening will not affect potency, however, suspensions with dark brown contents should be discarded.

17 PATIENT COUNSELING INFORMATION

Advise the patient to read the FDA-approved patient labeling (Instructions for Use).

Renal Impairment

Inform patients that sfROWASA may decrease their renal function, especially if they have known renal impairment or are taking nephrotoxic drugs, and periodic monitoring of renal function will be performed while they are on therapy. Advise patients to complete all blood tests ordered by their healthcare provider [see Warnings and Precautions (5.1)].

Mesalamine-Induced Acute Intolerance Syndrome and Other Hypersensitivity Reactions

Instruct patients to stop taking sfROWASA and report to their healthcare provider if they experience new or worsening symptoms of acute intolerance syndrome (cramping, abdominal pain, bloody diarrhea, fever, headache, and rash) or other symptoms suggestive of mesalamine-induced hypersensitivity [see Warnings and Precautions (5.2, 5.3)].

Hepatic Failure

Advise patients with known liver disease to contact their healthcare provider if they experience signs or symptoms of worsening liver function [see Warnings and Precautions (5.4)].

Severe Cutaneous Adverse Reactions

Inform patients of the signs and symptoms of severe cutaneous adverse reactions. Instruct patients to stop taking sfROWASA and report to their healthcare provider at first appearance of a severe cutaneous adverse reaction or other sign of hypersensitivity [see Warnings and Precautions (5.5)].

Photosensitivity

Advise patients with pre-existing skin conditions to avoid sun exposure, wear protective clothing, and use a broad-spectrum sunscreen when outdoors [see Warnings and Precautions (5.7)].

Nephrolithiasis

Instruct patients to drink an adequate amount of fluids during treatment in order to minimize the risk of kidney stone formation and to contact their healthcare provider if they experience signs or symptoms of a kidney stone (e.g., severe side or back pain, blood in the urine) [see Warnings and Precautions (5.7)].

Blood Disorders

Inform elderly patients and those taking azathioprine or 6-mercaptopurine of the risk for blood disorders and the need for periodic monitoring of complete blood cell counts and platelet counts while on therapy. Advise patients to complete all blood tests ordered by their healthcare provider [see Drug Interactions (7.2), Use in Specific Populations (8.5)].

Administration

Advise patients that sfROWASA will cause staining of direct contact surfaces, including but not limited to fabrics, flooring, painted surfaces, marble, granite, vinyl, and enamel. Administer the product in a suitable location.

Instruct patients:

- Shake the bottle to ensure the suspension is homogeneous.
- Remove the protective sheath from the applicator tip.
- Lie on the left side with the lower leg extended and the upper right leg flexed forward for balance. Alternatively, alternative is the knee-chest position.
- Gently insert the applicator tip in the rectum pointing toward the umbilicus.
- Steadily squeeze the bottle to discharge the medication.
- Administer at bedtime with the objective of retaining it all night.
- Drink an adequate amount of fluids during treatment [see Warnings and Precautions (5.7)].
- Advise patients that urine may become discolored reddish-brown while taking sfROWASA when it comes in contact with surfaces or water treated with hypochlorite-containing bleach. If discolored urine is observed, advise patients to observe their urine flow. Report to the healthcare provider only if urine is discolored on leaving the body, before contact with any surface or water (e.g., in the toilet).

IN-003260-08

Distributed by:
Meda Pharmaceuticals
Canonsburg, PA 15317 U.S.A.

© 2024 Viatris Inc.

sfROWASA is a registered
trademark of Alaven Pharmaceutical LLC, a Viatris Company.

For Medical Inquiries, Call Toll Free:
1-866-210-5949

INSTRUCTIONS FOR USE

sfROWASA® [s f ro wa sa]
(mesalamine)
rectal suspension sulfite-free formulation

This Instructions for Use contains information on how to use sfROWASA® (mesalamine) rectal suspension. Read these Instructions for Use that come with your sfROWASA (mesalamine) rectal suspension before you start using it and each time you get a refill. There may be new information. This information does not take the place of talking to your healthcare provider about your medical condition or your treatment.

How should I Store sfROWASA?

- Store sfROWASA at room temperature between 68°F to 77°F (20°C to 25°C).
- sfROWASA is an off-white to tan colored suspension. The medicine removed from the foil pouch may darken with time. Slight darkening will not affect how well sfROWASA works.
- Throw away sfROWASA (mesalamine) rectal suspensions with dark brown medicine.
- Keep sfROWASA and all medicines out of the reach of children.

Important Information You Need to Know Before Using sfROWASA

- sfROWASA is for rectal use only.
- Do not share sfROWASA with other people, it may harm them.
- If a caregiver is giving sfROWASA make sure they read and understand these Instructions for Use.
- Use sfROWASA exactly as your healthcare provider tells you to use it.
- It is recommended to use 1 sfROWASA bottle each day.
- After the foil wrapped unit of 7 bottles is opened, use each bottle of sfROWASA (mesalamine) rectal suspension right away.
- Empty bowels right before the medicine is given.
- Give at bedtime.
- sfROWASA will stain some surfaces including but not limited to fabrics, flooring, painted surfaces, marble, granite, vinyl, and enamel. Take care in choosing the right place for giving the sfROWASA (mesalamine) rectal suspension.

Preparing to use sfROWASA

Step 1. Remove the bottles.

- Remove all the bottles from the protective foil pouch by grasping at the seam and tearing downward or by using scissors at the top of the foil pouch (See Figure A).
- Be careful not to squeeze or puncture bottles.

Figure A

Step 2. Prepare to give the medicine.

- Shake the first bottle well to make sure that the medicine is mixed well.
- Remove the protective sheath from the applicator tip. Hold the bottle at the neck so as not to cause any of the medicine to be released (See Figure B).

Figure B

Step 3. Get in position.

- Lay on your left side with your left leg extended and your right leg flexed forward for balance (See Figure C).

Figure C

or

- Get in the knee-chest position as shown here (See Figure D).

Figure D

Step 4. Giving the medicine.

- Lubricate the applicator tip.
- Gently insert the lubricated applicator tip into the rectum pointing slightly toward the belly button (navel) to prevent damage to the rectal wall.
- Grasp the bottle firmly, then tilt slightly so that the nozzle is aimed toward the back.
- Squeeze the bottle slowly to release the medicine into the rectum (See Figure E).
- Steady hand pressure will release most of the medicine.

Figure E

- After giving the medicine, withdraw the applicator tip.
- Remain in position for at least 30 minutes to allow the medicine to spread inside the body.
- Throw away (discard) the bottle.
- Try to keep the medicine inside your body all night, if possible.

Distributed by:
Meda Pharmaceuticals
Canonsburg, PA 15317 U.S.A.

© 2024 Viatris Inc.
U.S. Patent No. 7,645,801
sfROWASA is a registered
trademark of Alaven Pharmaceutical LLC, a Viatris Company.

IN-003260-08

Rev. 7/2024

For Medical Inquiries, Call Toll Free:
1-866-210-5949

PRINCIPAL DISPLAY PANEL – 4 g/60 mL

NDC 0037-0022-07

7 X 60 mL Unit-Dose Bottles

sfROWASA®
(mesalamine)
rectal suspension, 4 g/60 Ml
Sulfite-Free Formulation

7 pack

For Rectal Use Only

Rx Only

Each disposable unit contains:
Mesalamine (5-aminosalicylic acid)........................................................4 grams
in suspension containing carbomer 934P, edetate disodium, potassium acetate,
purified water, sodium benzoate, and xanthan gum.

USUAL DOSE: One unit-dose suspension in the evenings before going to bed.
See package insert for complete prescribing information including usual dose.
See enclosed directions for use.
Use as directed by your physician.

KEEP THIS AND ANY MEDICATION OUT OF REACH OF CHILDREN.

SHAKE WELL BEFORE USING.

FOIL WRAP PROTECTS PRODUCT FROM DISCOLORATION. DO NOT REMOVE
PRODUCT FROM FOIL WRAP UNTIL READY TO USE.

Once the foil-wrapped unit of seven bottles is opened, any bottles remaining
after 14 days should be discarded.

Product contents may darken with time.

NOTE: product contents will cause staining of most direct contact surfaces.

Store at controlled room temperature 20° to 25°C (68° to 77°F); brief excursions
permitted 15° to 30°C (59° to 86°F) [See USP].

Dispensed in original foil-wrapped package.

For medical inquiries, call toll-free 1-866-210-5950.

SHAKE WELL BEFORE USING

Distributed by:
MEDA
PHARMACEUTICALS®
Canonsburg, PA 15317 U.S.A.

© 2024 Viatris Inc

SFROWASA is a registered trademark
of Alaven Pharmaceutical LLC,
a Viatris Company.

U.S. Patent No. 7,645,801

UC-003207-05

Rev. 8/2024